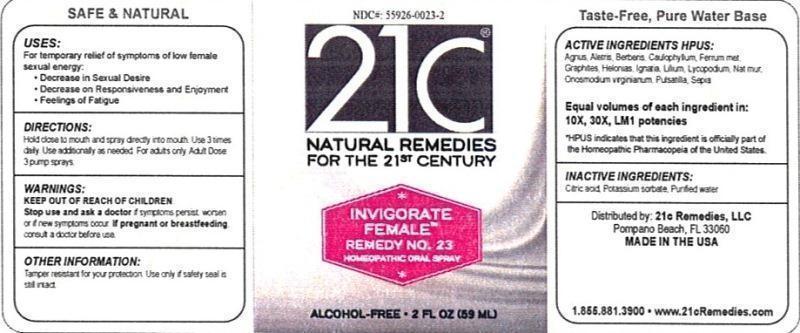 DRUG LABEL: Invigorate Female Remedy No. 23
NDC: 55926-0023 | Form: LIQUID
Manufacturer: Speer Laboratories, LLC
Category: homeopathic | Type: HUMAN OTC DRUG LABEL
Date: 20130730

ACTIVE INGREDIENTS: CHASTE TREE 10 [hp_X]/59 mL; ALETRIS FARINOSA ROOT 10 [hp_X]/59 mL; BERBERIS VULGARIS ROOT BARK 10 [hp_X]/59 mL; CAULOPHYLLUM THALICTROIDES ROOT 10 [hp_X]/59 mL; IRON 10 [hp_X]/59 mL; GRAPHITE 10 [hp_X]/59 mL; CHAMAELIRIUM LUTEUM ROOT 10 [hp_X]/59 mL; STRYCHNOS IGNATII SEED 10 [hp_X]/59 mL; LILIUM LANCIFOLIUM WHOLE FLOWERING 10 [hp_X]/59 mL; LYCOPODIUM CLAVATUM SPORE 10 [hp_X]/59 mL; SODIUM CHLORIDE 10 [hp_X]/59 mL; ONOSMODIUM VIRGINIANUM WHOLE 10 [hp_X]/59 mL; PULSATILLA VULGARIS 10 [hp_X]/59 mL; SEPIA OFFICINALIS JUICE 10 [hp_X]/59 mL
INACTIVE INGREDIENTS: WATER; CITRIC ACID MONOHYDRATE; POTASSIUM SORBATE

Invigorate Female Remedy No. 23

ACTIVE INGREDIENT

Active Ingredients HPUS: Agnus castus, Aletris farinosa, Berberis vulgaris, Caulopyllum thalictroides, Ferrum metallicum, Graphites, Helonias dioica, Ignatia amara, Lilium tigrinum, Lycopodium clavatum, Natrum muriaticum, Onosmodium virginianum, Pulsatilla, Sepia.

Equal volumes of each ingredient in: 10X, 30X, LM1 potencies. HPUS indicates that this ingredient is officially part of the Homeopathic Pharmacopeia of the United States.

Inactive Ingredients: Citric acid, Potassium sorbate, Purified water.

INDICATIONS AND USAGE

Uses: For temporary relief of symptoms of low female sexual energy:

- Decrease in sexual desire
- Decrease on responsiveness and enjoyment
- Feeling of fatigue

Directions:

Hold close to mouth and spray directly into mouth. Use 3 times daily. Use additionally as needed. For adults only. Adult dose 3 pump sprays

WARNINGS

Warnings: Stop use and ask a doctor if symptoms persist ,worsen or if new symptoms occur. If pregnant or breastfeeding, consult a doctor before use

Keep out of reach of children.

Other Information:

Tamper resistant for your protection. Use only if safety seal is still intact.

PURPOSE

Uses: For temporary relief of symptoms of low female sexual energy: decrease in sexual desire, decrease on responsiveness and enjoyment, feeling of fatigue.